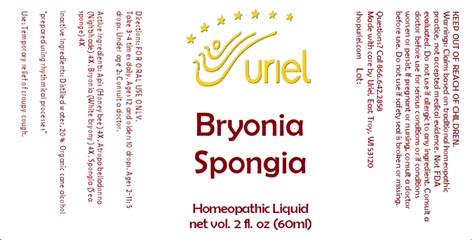 DRUG LABEL: Bryonia Spongia
NDC: 48951-2085 | Form: LIQUID
Manufacturer: Uriel Pharmacy Inc.
Category: homeopathic | Type: HUMAN OTC DRUG LABEL
Date: 20240326

ACTIVE INGREDIENTS: APIS MELLIFERA 4 [hp_X]/1 mL; ATROPA BELLADONNA 4 [hp_X]/1 mL; BRYONIA ALBA ROOT 4 [hp_X]/1 mL; SPONGIA OFFICINALIS WHOLE 4 [hp_X]/1 mL
INACTIVE INGREDIENTS: WATER; ALCOHOL

Bryonia Spongia

INDICATIONS AND USAGE

Directions: FOR ORAL USE ONLY.

DOSAGE AND ADMINISTRATION

Take 3-4 times daily. Ages 12 and older: 10 drops. Ages 2-11: 5 drops. Under age 2: Consult a doctor.

ACTIVE INGREDIENT

Active Ingredients: Apis (Honeybee) 4X, Atropa belladonna (Nightshade) 4X, Bryonia (White bryony) 4X, Spongia (Sea sponge) 4X

Inactive Ingredients: Distilled water, Organic cane alcohol

prepared using rhythmical processes

PURPOSE

Use: Temporary relief of croupy cough.

KEEP OUT OF REACH OF CHILDREN.

WARNINGS

Warnings: Claims based on traditional homeopathic practice, not accepted medical evidence. Not FDA evaluated. Do not use if allergic to any ingredient. Consult a doctor before use for serious conditions or if conditions worsen or persist. If pregnant or nursing, consult a doctor before use. Do not use if safety seal is broken or missing.

QUESTIONS

Questions? Call 866.642.2858 Made with care by Uriel, East Troy, WI 53120 shopuriel.com Lot: